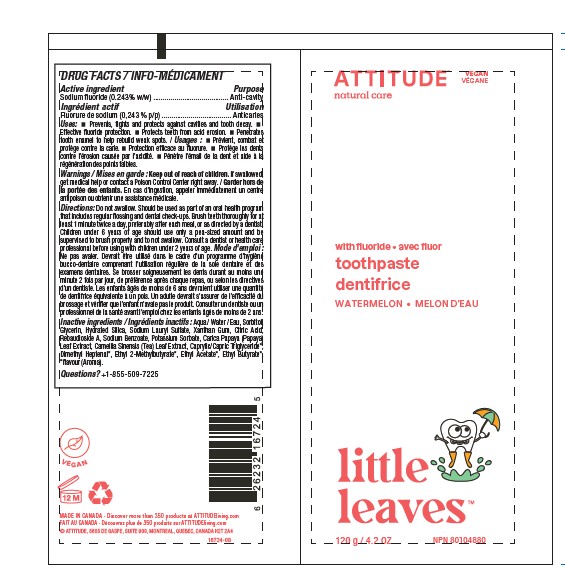 DRUG LABEL: BIO SPECTRA
NDC: 61649-724 | Form: GEL, DENTIFRICE
Manufacturer: 9055-7588 Québec Inc. DBA Attitude
Category: otc | Type: HUMAN OTC DRUG LABEL
Date: 20251020

ACTIVE INGREDIENTS: SODIUM FLUORIDE 0.243 g/100 g
INACTIVE INGREDIENTS: WATER; GLYCERIN; HYDRATED SILICA; SODIUM LAURYL SULFATE; XANTHAN GUM; ANHYDROUS CITRIC ACID; REBAUDIOSIDE A; SODIUM BENZOATE; CARICA PAPAYA LEAF; GREEN TEA LEAF; POTASSIUM SORBATE; MEDIUM-CHAIN TRIGLYCERIDES; ETHYL BUTYRATE; ETHYL 2-METHYLBUTYRATE; ETHYL ACETATE; 2,6-DIMETHYL-5-HEPTENAL; SORBITOL

ATTITUDE Little Leaves Toothpaste with Fluoride - Watermelon

DRUG FACTS

Active ingredient

Sodium fluoride (0.243% w/w)

Purpose

Anti-cavity

Uses

- Prevents, fights and protects against cavities and tooth decay.
- Effective fluoride protection.
- Protects teeth from acid erosion.
- Penetrates tooth enamel to help rebuild weak spots.

Warnings

Keep out of reach of children.

If swallowed, call a poison control centre or get medical help right away.

Directions

Do not swallow. Should be used as part of an oral health program that includes regular flossing and dental check-ups. Brush teeth thoroughly for at least 1 minute twice a day, preferably after each meal, or as directed by a dentist. Children under 6 years of age should use only a pea-sized amount and be supervised to brush properly and to not swallow. Consult a dentist or health care professional before using with children under 2 years of age. Store at room temperature (15-30 °C).

Inactive ingredients

Aqua / Water / Eau, Sorbitol, Glycerin, Hydrated Silica, Sodium Lauryl Sulfate, Xanthan Gum, Citric Acid, Rebaudioside A, Sodium Benzoate, Potassium Sorbate, Carica Papaya (Papaya) Leaf Extract, Camellia Sinensis (Tea) Leaf Extract, Caprylic/Capric Triglyceride*, Dimethyl Heptenal*, Ethyl 2-Methylbutyrate*, Ethyl Acetate*, Ethyl Butyrate*, *flavour (Aroma).

QUESTIONS?

+1-855-509-7225

PRINCIPAL DISPLAY PANEL - 120 g Tube Label

ATTITUDE™
natural care

vegan

with fluoride

toothpaste
watermelon
Little Leaves

NPN 80104880

120 g / 4.2 OZ.